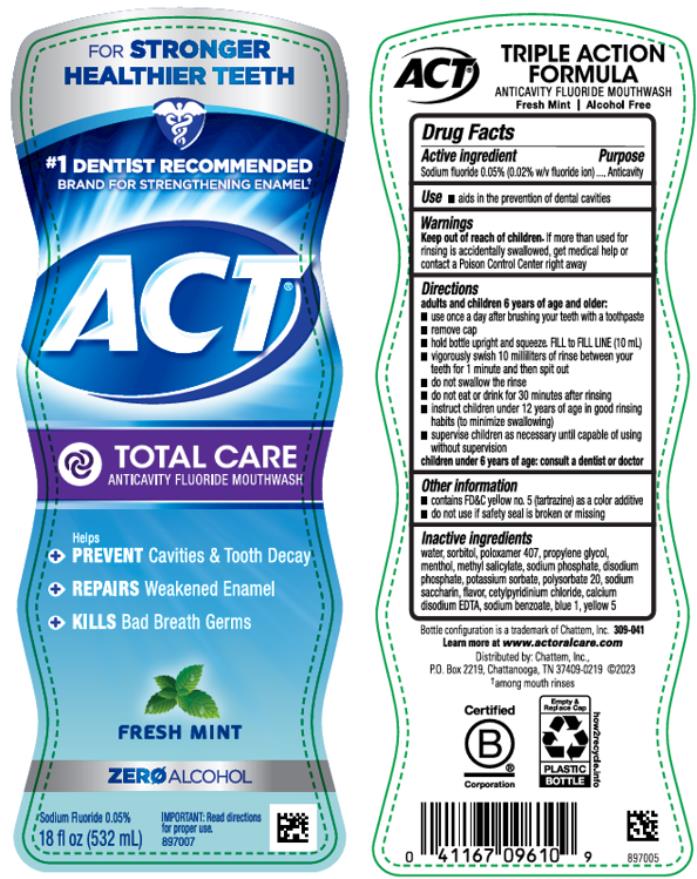 DRUG LABEL: ACT Total Care Anticavity Fluoride Fresh Mint
NDC: 41167-0961 | Form: RINSE
Manufacturer: Chattem, Inc.
Category: otc | Type: HUMAN OTC DRUG LABEL
Date: 20240801

ACTIVE INGREDIENTS: SODIUM FLUORIDE 0.2 mg/1 mL
INACTIVE INGREDIENTS: FD&C BLUE NO. 1; EDETATE CALCIUM DISODIUM ANHYDROUS; CETYLPYRIDINIUM CHLORIDE; MENTHOL; METHYL SALICYLATE; POLYSORBATE 20; POTASSIUM SORBATE; PROPYLENE GLYCOL; SODIUM BENZOATE; SODIUM PHOSPHATE; SACCHARIN SODIUM; FD&C YELLOW NO. 5; WATER; SORBITOL; POLOXAMER 407

ACT Total Care Anticavity Fluoride Rinse Fresh Mint

Drug Facts

Active ingredient

Sodium fluoride 0.02% (0.009% w/v fluoride ion)

Purpose

Anticavity

Use

- aids in the prevention of dental cavities

Warnings

Keep out of reach of children.

If more than used for rinsing is accidentally swallowed, get medical help or contact a Poison Control Center right away.

Directions

adults and children 6 years of age and older:

- use twice a day after brushing your teeth with a toothpaste
- remove cap
- pour 10 milliliters (10 mL mark on inside of cap); do not fill above 10 mL mark
- vigorously swish 10 milliliters of rinse between your teeth for 1 minute and then spit out
- do not swallow the rinse
- do not eat or drink for 30 minutes after rinsing
- instruct children under 12 years of age in good rinsing habits (to minimize swallowing)
- supervise children as necessary until capable of using without supervision

children under 6 years of age: consult a dentist or doctor

Other information

- contains FD&C yellow no. 5 (tartrazine) as a color additive
- do not use if safety seal is broken or missing

Inactive ingredients

water, sorbitol, poloxamer 407, propylene glycol, menthol, methyl salicylate, sodium phosphate, disodium phosphate, potassium sorbate, polysorbate 20, sodium saccharin, flavor, cetylpyridinium chloride, calcium disodium EDTA, sodium benzoate, blue 1, yellow 5

Learn more at www. ACTFLUORIDE.com

PRINCIPAL DISPLAY PANEL

FOR STRONGER
HEALTHIER TEETH
#1 DENTIST RECOMMENDED
BRAND FOR STRENGTHENING ENAMEL
ACT
TOTAL CARE
ANTICAVITY FLUORIDE MOUTHWASH
FRESH MINT
ZERO ALCOHOL
18 fl oz (532 mL)